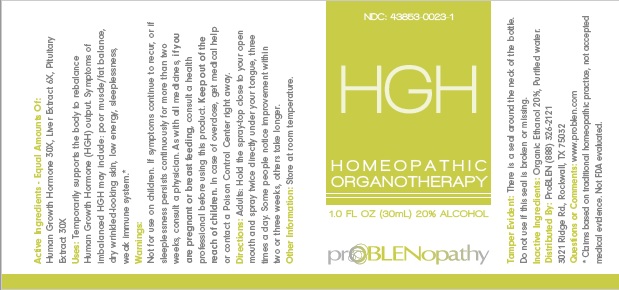 DRUG LABEL: HGH
NDC: 43853-0023 | Form: LIQUID
Manufacturer: ProBLEN
Category: homeopathic | Type: HUMAN OTC DRUG LABEL
Date: 20221130

ACTIVE INGREDIENTS: SOMATROPIN 30 [hp_X]/30 mL
INACTIVE INGREDIENTS: ALCOHOL; WATER

HGH

Active Ingredients - Equal Amounts Of:
Human Growth Hormone 30X, Liver Extract 6X, Pituitary Extract 30X.

* Claims based on traditional homeopathic practice, not accepted medical evidence. Not FDA evaluated

INDICATIONS AND USAGE

Uses: Temporarily supports the body to rebalance Human Growth Hormone (HGH) output. Symptoms of imbalanced HGH may include: poor muscle/fat balance, dry wrinkled-looking skin, low energy, sleeplessness, weak immune system.*

Warnings:
Not for use on children. If symptoms continue to recur, or if sleeplessness persists continuously for more than two weeks, consult a physician. As with all medicines, if you are pregnant or breast feeding, consult a health professional before using this product. Keep out of the reach of children. In case of overdose, get medical help or contact a Poison Control Center right away.

Keep out of the reach of children.

DOSAGE AND ADMINISTRATION

Directions: Adults: Hold the spray-top close to your open mouth and spray twice directly under your tongue, three times a day. Some people notice improvement within two or three weeks, others take longer.

Other Information: Store at room temperature.

Tamper Evident: There is a seal around the entire bottle. Do not use if this seal is broken or missing.

Inactive Ingredients: Organic Ethanol, Purified Water.

QUESTIONS

Distributed By: ProBLEN (888) 326-2121 3021 Ridge Rd., Rockwall, TX 75032
Questions or Comments: www.problen.com

PACKAGE LABEL

NDC: 43853-0023-1

HGH

HOMEOPATHIC

ORGANOTHERAPY

1.0 FL OZ (30mL) 20% ALCOHOL

prOBLENopathy

PURPOSE

Temporarily supports the body to rebalance Human Growth Hormone (HGH) output. Symptoms of imbalanced HGH may include: poor muscle/fat balance, dry wrinkled-looking skin, low energy, sleeplessness, weak immune system.*